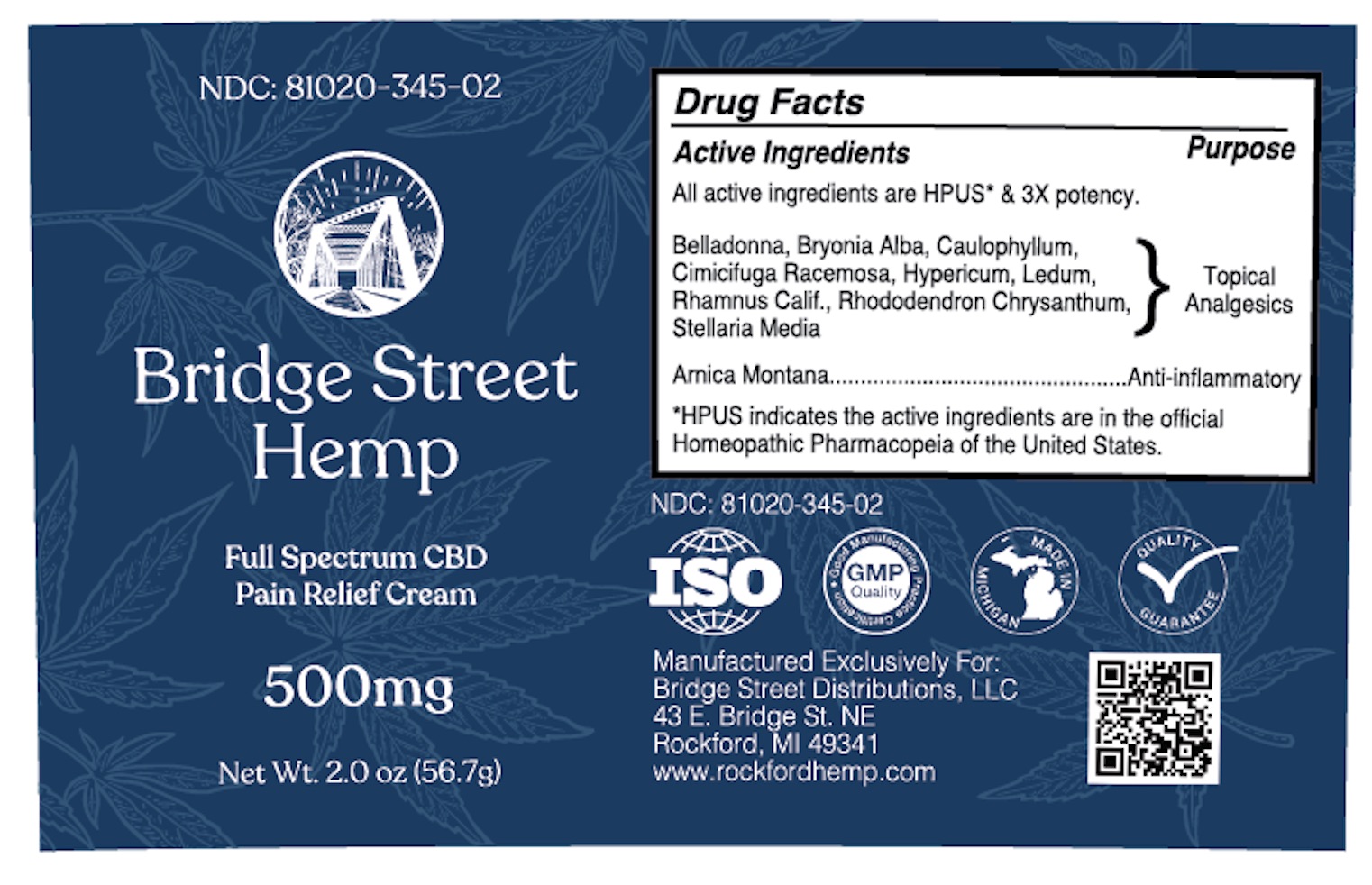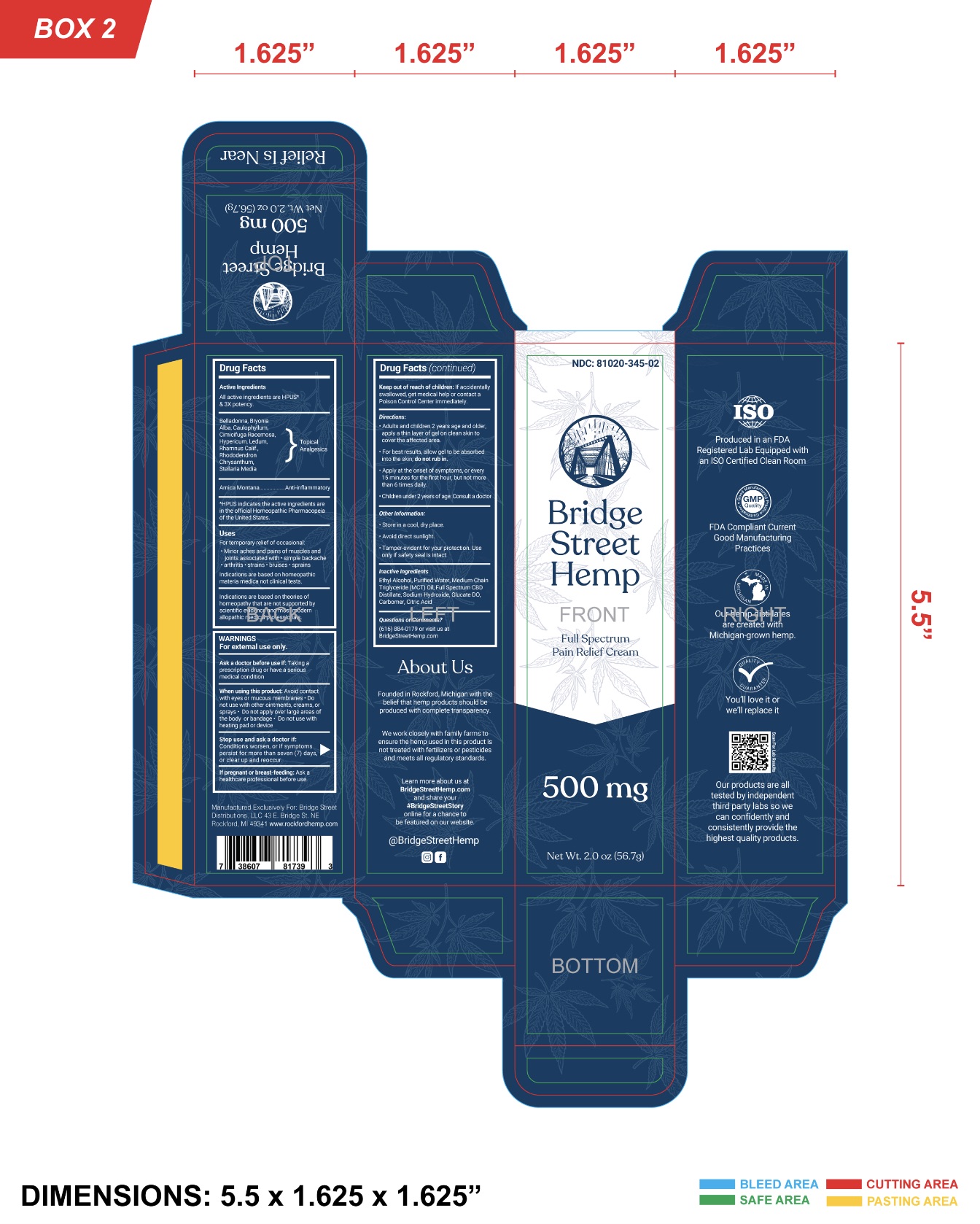 DRUG LABEL: Bridge Street Hemp Full Spectrum Pain Relief Cream
NDC: 81020-345 | Form: CREAM
Manufacturer: Vapejoose, Inc.
Category: homeopathic | Type: HUMAN OTC DRUG LABEL
Date: 20210121

ACTIVE INGREDIENTS: ARNICA MONTANA 3 [hp_X]/1 g; BLACK COHOSH 3 [hp_X]/1 g; STELLARIA MEDIA 3 [hp_X]/1 g; ATROPA BELLADONNA 3 [hp_X]/1 g; BRYONIA ALBA ROOT 3 [hp_X]/1 g; FRANGULA CALIFORNICA BARK 3 [hp_X]/1 g; RHODODENDRON AUREUM LEAF 3 [hp_X]/1 g; RHODODENDRON TOMENTOSUM LEAFY TWIG 3 [hp_X]/1 g; HYPERICUM PERFORATUM 3 [hp_X]/1 g; CAULOPHYLLUM THALICTROIDES ROOT 3 [hp_X]/1 g
INACTIVE INGREDIENTS: ANHYDROUS CITRIC ACID; WATER; MEDIUM-CHAIN TRIGLYCERIDES; METHYL GLUCOSE DIOLEATE; SODIUM HYDROXIDE; CARBOMER INTERPOLYMER TYPE A (ALLYL SUCROSE CROSSLINKED); CANNABIDIOL

Active Ingredients

All active ingredients are HPUS* & 3X potency.

Topical Analgesics - Belladonna, Bryonia Alba, Caulophyllum, Cimicifuga Racemosa, Hypericum, Ledum, Rhamnus Calif., Rhododendron Chrystanthum, Stellaria Media

Arnica Montana........Anti-inflammatory

*HPUS indicates the active ingredients are in the official Homoeopathic Pharmacopeia of the United States.

Uses

For temporary relief of occasional:

• minor aches and pains of muscles and joints associated with

• simple backache • arthritis • strains • bruises • sprains

Indications are based on homeopathic materia medica not clinical tests.

Indications are based on theories of homeopathy that are not supported by scientific evidence and most modern allopathic medical professionals.

Warnings

For external use only.

Ask a doctor before use if:

Taking a prescription drug or have a serious medical treatment.

When using this product:

Avoid contact with eyes or mucous membranes • Do not use with other ointments, creams, or sprays • Do not apply over large areas of the body or bandage • Do not use with heating pad or device

Stop use and ask a doctor if:

Conditions worsen, or if symptoms persist for more than seven (7) days, or clear up and reoccur.

If pregnant or breast-feeding:

ask a healthcare professional before use.

Keep out of reach of children:

if accidentally swallowed, get medical help or contact a Poison Control Center immediately.

Directions:

• Adults and children 2 years of age and older, apply a thin layer of gel on clean skin to cover the affected area.

• For best results, allow gel to be absorbed into the skin; do not rub in.

• Apply at the onset of symptoms, or every 15 minutes for the first hour, but not more than 6 times daily.

• Children under 2 years of age: Consult a doctor

Other Information

• Store in a cool, dry place.

• Avoid direct sunlight.

• Tamper-evident for your protection. Use only if safety seal is intact.

Inactive Ingredients

Ethyl Alchohol, Purified Water, Medium Chain Triglyceride (MCT) Oil, Full Spectrum CBD Distillate, Sodium Hydroxide, Glucate DO, Carbomer, Citric Acid

Questions or Comments?

(616) 884-0179 or visit us at BridgeStreetHemp.com